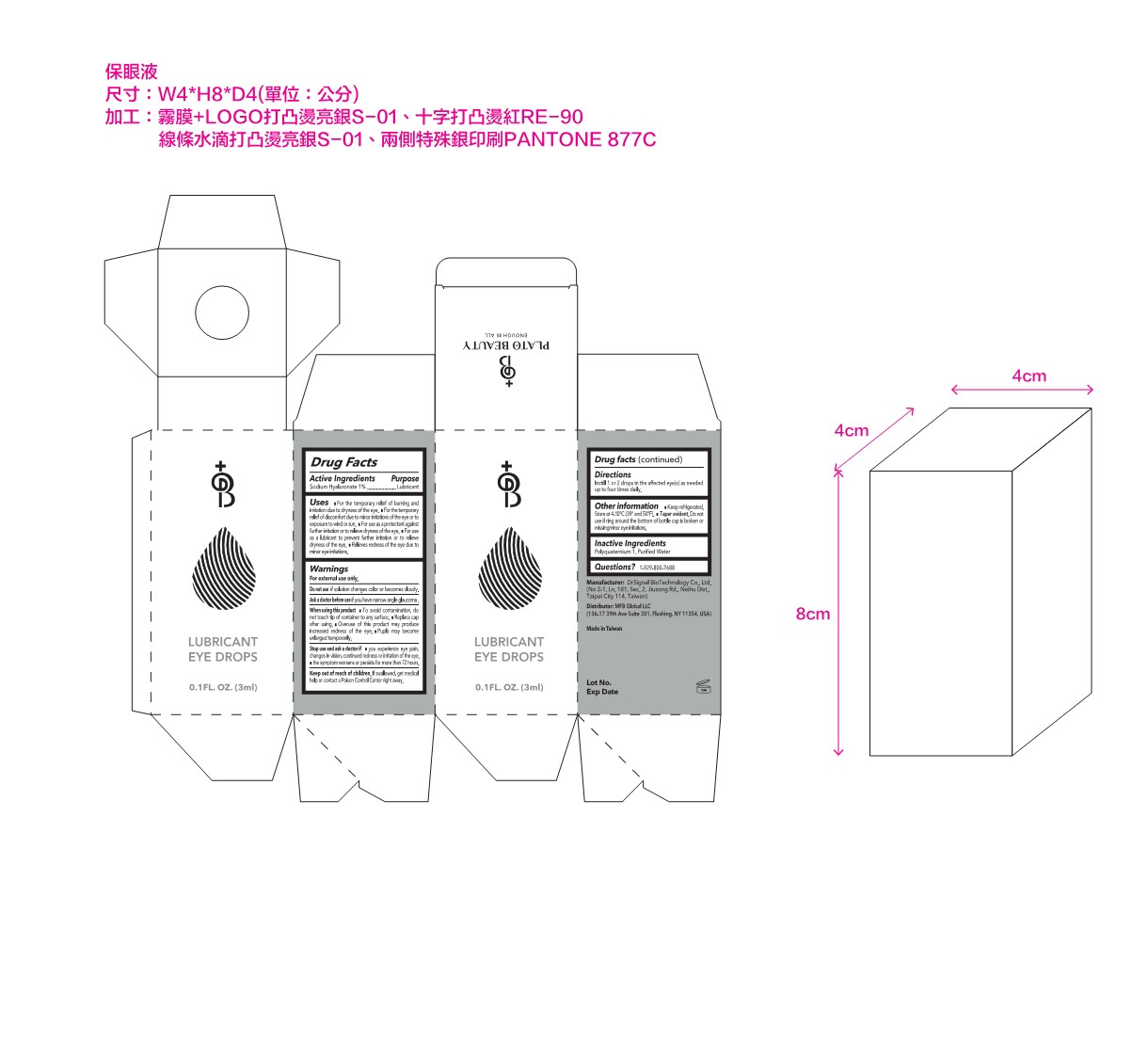 DRUG LABEL: Lubricant Eye Drops
NDC: 82357-1101 | Form: SOLUTION/ DROPS
Manufacturer: MFB Global LLC
Category: otc | Type: HUMAN OTC DRUG LABEL
Date: 20211107

ACTIVE INGREDIENTS: HYALURONATE SODIUM 3 g/100 mL; PYRIDOXINE HYDROCHLORIDE 0.3 g/100 mL
INACTIVE INGREDIENTS: WATER; POLIDRONIUM CHLORIDE

ACTIVE INGREDIENT

Sodium Hyaluronate 1%

PURPOSE

Lubricant

DOSAGE AND ADMINISTRATION

For the temporary relief of burning and irritation due to dryness of the eye.

For the temporary relief of discomfort due to minor irritations of the eye or to exposure to wind or sun.

For use as a protectant against further irritation or to relieve dryness of the eye.

For use as a lubricant to prevent further irritation or to relieve dryness of the eye.

Relieves redness of the eye due to minor eye irritations.

WARNINGS

For external use only

DO NOT USE

if solution changes color or becomes cloudy.

USER SAFETY WARNINGS

if you have narrow angle glaucoma.

WHEN USING

To avoid contamination, do not touch tip of container to any surface. ■ Replace cap after using. ■ Overuse of this product may produce increased redness of the eye. ■ Pupils may become enlarged temporarily.

ASK DOCTOR

if ■ you experience eye pain, changes in vision, continued redness or irritation of the eye. ■ the symptom worsens or persists for more than 72 hours.

KEEP OUT OF REACH OF CHILDREN

If swallowed, get medical help of contact a Poison Control Center right away.

INDICATIONS AND USAGE

Instill 1 or 2 drops in the affected eye(s) as needed up to four times daily.

OTHER SAFETY INFORMATION

Keep refrigerated. Store at 4-10℃(39-50℉). ■ Tamper Evident. Do not use if ring around the bottom of bottle cap is broken or missingminor eye irritations.

INACTIVE INGREDIENT

Polyquaternium 1

Purified Water.

PATIENT COUNSELING INFORMATION

1-646-339-5789

Manufacturer: DrSignal BioTechnology Co., Ltd. (No. 2-1, Ln. 181, Sec. 2, Jiuzong Rd., Neihu Dist., Taipei City 114, Taiwan)
Distributor: MFB Global LLC
(136-17 39th Ave Suite 301, Flushing, NY 11354, USA) Tel: 1-646-339-5789

Made in Taiwan

DESCRIPTION

product information